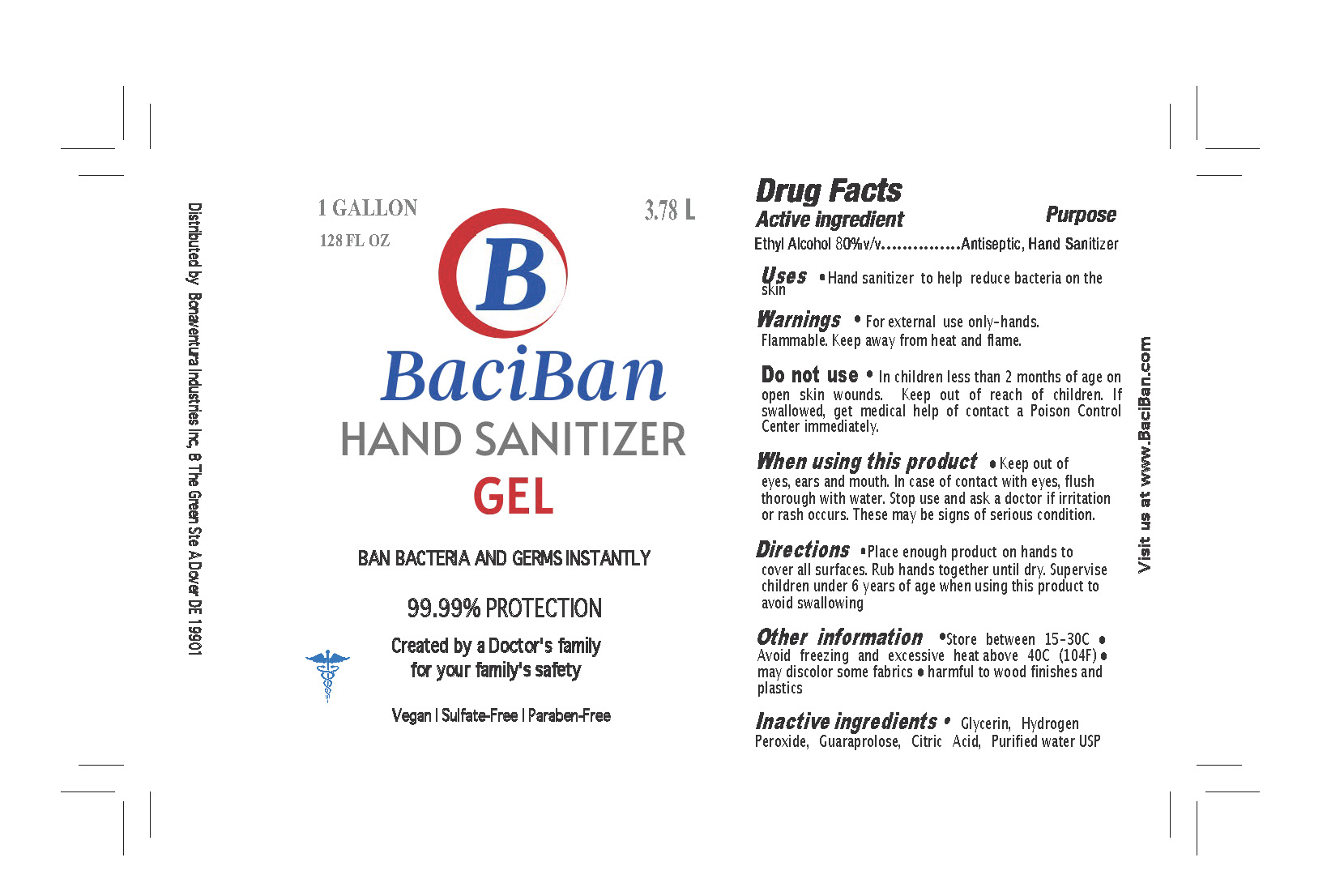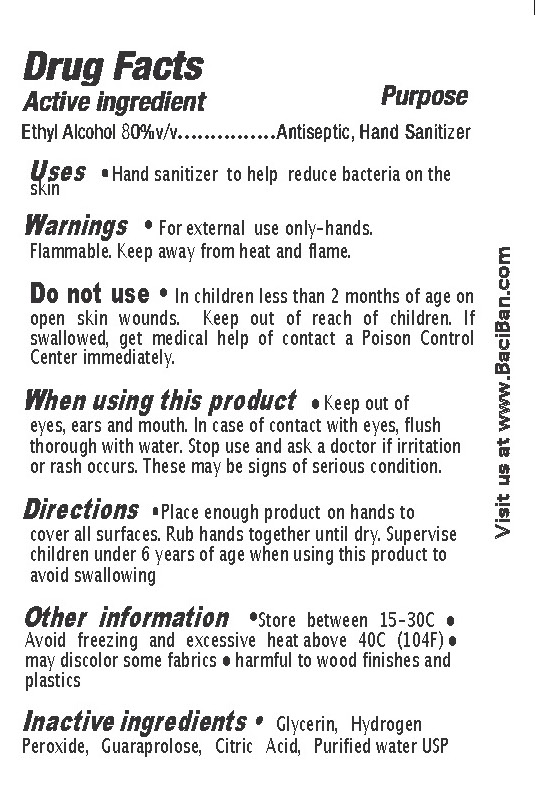 DRUG LABEL: BaciBan
NDC: 77330-003 | Form: GEL
Manufacturer: Bonaventura Industries Inc
Category: otc | Type: HUMAN OTC DRUG LABEL
Date: 20200822

ACTIVE INGREDIENTS: ALCOHOL 80 mL/100 mL
INACTIVE INGREDIENTS: CITRIC ACID MONOHYDRATE; WATER; GLYCERIN 1.45 mL/100 mL; GUARAPROLOSE (3500 MPA.S AT 1%); HYDROGEN PEROXIDE 0.125 mL/100 mL

BaciBan Gel

Active ingredient

Ethyl Alcohol 80%

Purpose

Antiseptic, Hand Sanitizer

Uses

Hand sanitizer to help reduce bacteria on the hands

Warnings

For external use only-hands.

Flammable. Keep away from heat and flame. Do not use in

children less than 2 months of age on open skin wounds

Do Not Use

- in children less than 2 months of age
- on open skin wounds

When using this product

Keep out of eyes, ears, and mouth.

In case of contact with eyes, flush thoroughly with water.

Directions

Place enough product on hands to cover all surfaces.

Rub hands together until dry.

Supervise children under 6 years of age when using this product to avoid swallowing

Other Information

•Store between 15-30C

• Avoid freezing and excessive heat above 40C (104F)

• may discolor some fabrics • harmful to wood finishes and plastics

Inactive Ingredients

Glycerin, Hydrogen Peroxide, Guaraprolose, Citric Acid, Purified Water USP

Stop use and ask a doctor if irritation or rash occurs. These may be signs of serious condition.

Keep out of reach of children. If swallowed, get medical help of contact a Poison Control Center immediately.